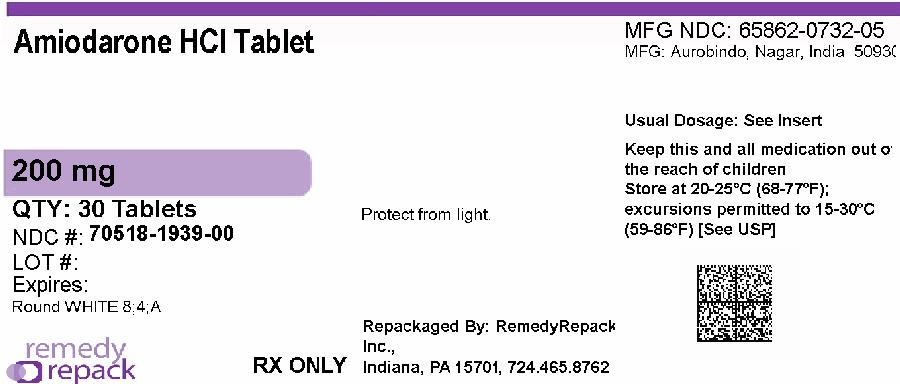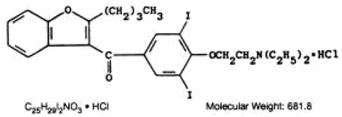 DRUG LABEL: Amiodarone Hydrochloride
NDC: 70518-1939 | Form: TABLET
Manufacturer: REMEDYREPACK INC.
Category: prescription | Type: HUMAN PRESCRIPTION DRUG LABEL
Date: 20260220

ACTIVE INGREDIENTS: AMIODARONE HYDROCHLORIDE 200 mg/1 1
INACTIVE INGREDIENTS: SILICON DIOXIDE; LACTOSE MONOHYDRATE; MAGNESIUM STEARATE; POVIDONE K30; SODIUM STARCH GLYCOLATE TYPE A POTATO

HIGHLIGHTS OF PRESCRIBING INFORMATION

These highlights do not include all the information needed to use AMIODARONE HYDROCHLORIDE TABLETS safely and effectively. See full prescribing information for AMIODARONE HYDROCHLORIDE TABLETS.
AMIODARONE HYDROCHLORIDE tablets, for oral use
Initial U.S. Approval: 1985

WARNING: PULMONARY, HEPATIC and CARDIAC TOXICITY

See full prescribing information for complete boxed warning.

- Reserve amiodarone hydrochloridefor patients with the indicated life-threatening arrhythmias because its use is accompanied by substantial toxicity, some also life-threatening. Utilize alternative agents first. (1)
- Amiodarone hydrochloride’s life-threatening toxicities include pulmonary (5.2), hepatic (5.3), and proarrhythmic (5.4).
- Initiate under hospital or specialist supervision. (5)

1 INDICATIONS AND USAGE

Amiodarone hydrochloride is an antiarrhythmic indicated for:

- Recurrent ventricular fibrillation. (1)
- Recurrent hemodynamically unstable ventricular tachycardia. (1)

2 DOSAGE AND ADMINISTRATION

Initiate treatment with a loading doses of 800 to 1600 mg/day until initial therapeutic response occurs (usually 1 to 3 weeks). Once adequate arrhythmia control is achieved, or if side effects become prominent, reduce amiodarone hydrochloride dose to 600 to 800 mg/day for one month and then to the maintenance dose, usually 400 mg/day. (2)

3 DOSAGE FORMS AND STRENGTHS

Tablets, 200 mg. (3)

4 CONTRAINDICATIONS

Amiodarone hydrochloride tablets are contraindicated in patients with (4):

- Cardiogenic shock.
- Sick sinus syndrome, second- or third-degree AV block, bradycardia leading to syncope without a functioning pacemaker.
- Known hypersensitivity to the drug or any of its components.

5 WARNINGS AND PRECAUTIONS

- Persistence of Adverse Effects: Adverse reactions and drug interaction can persist for several weeks following discontinuation. (5.1)
- Impaired Vision: Corneal microdeposits (common; reversible), optic neuropathy/neuritis (rare; may lead to blindness). (5.5)
- Thyroid Abnormalities: Hyperthyroidism or hypothyroidism. (5.6)

6 ADVERSE REACTIONS

- The most common reactions (>1%) leading to discontinuation of amiodarone hydrochloride include pulmonary toxicity, paroxysmal ventricular tachycardia, congestive heart failure, and elevation of liver enzymes. (6)

To report SUSPECTED ADVERSE REACTIONS, contact Aurobindo Pharma USA, Inc. at 1-866-850-2876 or FDA at 1-800-FDA-1088 orwww.fda.gov/medwatch.

7 DRUG INTERACTIONS

- Avoid coadministration of amiodarone with other antiarrhythmics and drugs known to prolong the QT interval. (7)
- Amiodarone is a substrate for CYP3A and CYP2C8, so inhibitors and inducers affect amiodarone exposure. (7)
- Amiodarone inhibits P-glycoprotein and CYP1A2, CYP2C9, CYP2D6, and CYP3A, increasing exposure to other drugs. (7)

8 USE IN SPECIFIC POPULATIONS

- Pregnancy: May cause fetal harm. (8.1)
- Lactation: Breastfeeding not recommended. (8.2)

FULL PRESCRIBING INFORMATION

WARNING: PULMONARY, HEPATIC and CARDIAC TOXICITY

Amiodarone hydrochlorideis intended for use only in patients with the indicated life-threatening arrhythmias because its use is accompanied by substantial toxicity [see Indications and Usage (1)].
Amiodarone hydrochloride can cause pulmonary toxicity (hypersensitivity pneumonitis or interstitial/alveolar pneumonitis) that has resulted in clinically manifest disease at rates as high as 17% in some series of patients. Pulmonary toxicity has been fatal about 10% of the time. Obtain a baseline chest X-ray and pulmonary-function tests, including diffusion capacity, when amiodarone hydrochloridetherapy is initiated. Repeat history, physical exam, and chest X-ray every 3 to 6 months [see Warnings and Precautions 5.2)].
Amiodarone hydrochloride can cause hepatoxicity, which can be fatal. Obtain baseline and periodic liver transaminases and discontinue or reduce dose if the increase exceeds three times normal, or doubles in a patient with an elevated baseline. Discontinue amiodarone hydrochlorideif the patient experiences signs or symptoms of clinical liver injury [see Warnings and Precautions (5.3)] .
Amiodarone hydrochloride can exacerbate arrhythmias. Initiate amiodarone hydrochloridein a clinical setting where continuous electrocardiograms and cardiac resuscitation are available [see Warnings and Precautions (5.4)].

1 INDICATIONS AND USAGE

Amiodarone hydrochloride tablets are indicated for the treatment of documented, life-threatening recurrent ventricular fibrillation and life-threatening recurrent hemodynamically unstable tachycardia in adults who have not responded to adequate doses of other available antiarrhythmics or when alternative agents cannot be tolerated.

2 DOSAGE AND ADMINISTRATION

Dosage must be individualized based on severity of arrhythmia and response. Use the lowest effective dose. Obtain baseline chest x-ray, pulmonary function tests, thyroid function tests, and liver aminotransferases. Correct hypokalemia, hypomagnesemia, and hypocalcemia before initiating treatment
Recommended Dosage:

Initiate treatment with a loading doses of 800 to 1600 mg/day until initial therapeutic response occurs (usually 1 to 3 weeks). Once adequate arrhythmia control is achieved, or if side effects become prominent, reduce amiodarone hydrochloride dose to 600 to 800 mg/day for one month and then to the maintenance dose, usually 400 mg/day.

Administration:

Administer amiodarone hydrochloride tablets consistently with regard to meals [see Clinical Pharmacology (12.3)] . Administration of amiodarone hydrochloride tablets in divided doses with meals is suggested for total daily doses of 1000 mg or higher, or when gastrointestinal intolerance occurs.

3 DOSAGE FORMS AND STRENGTHS

Amiodarone Hydrochloride Tablets USP, 200 mgare white to off-white, round biconvex uncoated tablets debossed with “8” and “4” separated by a breakline on one side and “A” on the other side.

4 CONTRAINDICATIONS

- Cardiogenic shock.
- Sick sinus syndrome, second- or third-degree atrioventricular block, bradycardia leading to syncope without a functioning pacemaker.
- Known hypersensitivity to the drug or to any of its components, including iodine.

5 WARNINGS AND PRECAUTIONS

5.1 Persistence of Adverse Effects

Because of the long half-life of amiodarone (15 to 142 days) and its active metabolite desethylamiodarone (14 to 75 days), adverse reactions and drug interactions can persist for several weeks following amiodarone discontinuation [see Clinical Pharmacology (12.3)] .

5.2 Pulmonary Toxicity

Amiodarone hydrochloride may cause a clinical syndrome of cough and progressive dyspnea accompanied by functional, radiographic, gallium-scan, and pathological data consistent with pulmonary toxicity. Pulmonary toxicity secondary to amiodarone hydrochloride may result from either indirect or direct toxicity as represented by hypersensitivity pneumonitis (including eosinophilic pneumonia) or interstitial/alveolar pneumonitis, respectively. Rates of pulmonary toxicity have been reported to be as high as 17% and is fatal in about 10% of cases. Obtain a baseline chest X-ray and pulmonary-function tests, including diffusion capacity, when amiodarone hydrochloride therapy is initiated. Repeat history, physical exam, and chest X-ray every 3 to 6 months or if symptoms occur. Consider alternative antiarrhythmic therapy if the patient experiences signs or symptoms of pulmonary toxicity. Prednisone 40 to 60 mg/day tapered over several weeks may be helpful in treating pulmonary toxicity.
Adult Respiratory Distress Syndrome (ARDS)
Postoperatively, occurrences of ARDS have been reported in patients receiving amiodarone hydrochloride therapy who have undergone either cardiac or noncardiac surgery. Although patients usually respond well to vigorous respiratory therapy, in rare instances the outcome has been fatal.

5.3 Hepatic Injury

Asymptomatic elevations of hepatic enzyme levels are seen frequently, but amiodarone hydrochloride can cause life-threatening hepatic injury. Histology has resembled that of alcoholic hepatitis or cirrhosis. Obtain baseline and periodic liver transaminases. If transaminases exceed three times normal, or doubles in a patient with an elevated baseline, discontinue or reduce dose of amiodarone hydrochloride, obtain follow-up tests and treat appropriately.

5.4 Worsened Arrhythmia

Amiodarone hydrochloride can exacerbate the presenting arrhythmia in about 2 to 5% of patients or cause new ventricular fibrillation, incessant ventricular tachycardia, increased resistance to cardioversion, and polymorphic ventricular tachycardia associated with QTc prolongation (Torsade de Pointes [TdP]).

Correct hypokalemia, hypomagnesemia, and hypocalcemia before initiating treatment with amiodarone hydrochloride, as these disorders can exaggerate the degree of QTc prolongation and increase the potential for TdP. Give special attention to electrolyte and acid-base balance in patients experiencing severe or prolonged diarrhea or receiving drugs affecting electrolyte levels, such as diuretics, laxatives, systemic corticosteroids, or amphotericin B.

5.5 Visual Impairment and Loss of Vision

Optic Neuropathy and Optic Neuritis
Cases of optic neuropathy and optic neuritis, usually resulting in visual impairment and sometimes permanent blindness, have been reported in patients treated with amiodarone and may occur at any time during therapy. If symptoms of visual impairment appear, such as changes in visual acuity and decreases in peripheral vision, consider discontinuing amiodarone hydrochloride and promptly refer for ophthalmic examination. Regular ophthalmic examination, including funduscopy and slit-lamp examination, is recommended during administration of amiodarone hydrochloride [see Adverse Reactions (6.1)].
Corneal Microdeposits
Corneal microdeposits appear in the majority of adults treated with amiodarone hydrochloride. They are usually discernible only by slit-lamp examination, but give rise to symptoms such as visual halos or blurred vision in as many as 10% of patients. Corneal microdeposits are reversible upon reduction of dose or termination of treatment. Asymptomatic microdeposits alone are not a reason to reduce dose or discontinue treatment [see Adverse Reactions (6.1)].

5.6 Thyroid Abnormalities

Amiodarone hydrochloride inhibits peripheral conversion of thyroxine (T4) to triiodothyronine (T3) and may cause increased thyroxine levels, decreased T3levels, and increased levels of inactive reverse T3(rT3) in clinically euthyroid patients. Amiodarone hydrochloride can cause either hypothyroidism (reported in up to 10% of patients) or hyperthyroidism (occurring in about 2% of patients). Monitor thyroid function prior to treatment and periodically thereafter, particularly in elderly patients, and in any patient with a history of thyroid nodules, goiter, or other thyroid dysfunction.

Hyperthyroidism mayinduce arrhythmia breakthrough. If any new signs of arrhythmia appear, the possibility of hyperthyroidism should be considered. Antithyroid drugs, β-adrenergic blockers, temporary corticosteroid therapy may be necessary to treat the symptoms of hyperthyroidism. The action of antithyroid drugs may be delayed in amiodarone-induced thyrotoxicosis because of substantial quantities of preformed thyroid hormones stored in the gland. Radioactive iodine therapy is contraindicated because of the low radioiodine uptake associated with amiodarone-induced hyperthyroidism. Amiodarone hydrochloride-induced hyperthyroidism may be followed by a transient period of hypothyroidism.

Hypothyrodism may be primary or subsequent to resolution of preceding amiodarone-induced hyperthyroidism. Severe hypothyroidism and myxedema coma, sometimes fatal, have been reported in association with amiodarone therapy. In some clinically hypothyroid amiodarone-treated patients, free thyroxine index values may be normal. Manage hypothyroidism by reducing the dose of or discontinuing amiodarone hydrochloride and thyroid hormone supplementation.

5.7 Bradycardia

Amiodarone hydrochloride causes symptomatic bradycardia or sinus arrest with suppression of escape foci in 2 to 4% of patients. The risk is increased by electrolytic disorders or use of concomitant antiarrhythmics or negative chronotropes [see Drug Interactions (7)] . Bradycardia may require a pacemaker for rate control.
Postmarketing cases of symptomatic bradycardia, some requiring pacemaker insertion and at least one fatal, have been reported when ledipasvir/sofosbuvir or sofosbuvir with simeprevir were initiated in patients on amiodarone. Bradycardia generally occurred within hours to days, but in some cases presented up to 2 weeks after initiating antiviral treatment. Bradycardia generally resolved after discontinuation of antiviral treatment. The mechanism for this effect is unknown. Monitor heart rate in patients taking or recently discontinuing amiodarone when starting antiviral treatment [see Drug Interactions (7)].

5.8 Implantable Cardiac Devices

In patients with implanted defibrillators or pacemakers, chronic administration of antiarrhythmic drugs may affect pacing or defibrillation thresholds. Therefore, at the inception of and during amiodarone treatment, pacing and defibrillation thresholds should be assessed.

5.9 Fetal Toxicity

Amiodarone hydrochloride may cause fetal harm when administered to a pregnant woman. Fetal exposure may increase the potential for cardiac, thyroid, neurodevelopmental, neurological, and growth effects in neonate [see Use in Specific Populations (8.1)].

5.10 Peripheral Neuropathy

Chronic administration of amiodarone hydrochloride may lead to peripheral neuropathy, which may not resolve when amiodarone hydrochloride is discontinued.

5.11 Photosensitivity and Skin Discoloration

Amiodarone hydrochloride induces photosensitization in about 10% of patients; some protection may be afforded sun-barrier creams or protective clothing. During long-term treatment, a blue-gray discoloration of the exposed skin may occur. The risk may be increased in patients of fair complexion or those with excessive sun exposure. Some reversal of discoloration may occur upon drug discontinuation.

5.12 Surgery

Volatile Anesthetic Agents
Patients on amiodarone hydrochloride therapy may be more sensitive to the myocardial depressant and conduction effects of halogenated inhalational anesthetics.

6 ADVERSE REACTIONS

The following serious adverse reactions are described in more detail in other sections of the prescribing information:

- Pulmonary Toxicity [see Warnings and Precautions (5.2)]
- Hepatic Injury [see Warnings and Precautions (5.3)]
- Worsened Arrhythmia [see Warnings and Precautions (5.4)]
- Visual Impairment and Loss of Vision [see Warnings and Precautions (5.5)]
- Thyroid Abnormalities [see Warnings and Precautions (5.6)]
- Bradycardia [see Warnings and Precautions (5.7)]
- Peripheral Neuropathy [see Warnings and Precautions (5.10)]
- Photosensitivity and Skin Discoloration [see Warnings and Precautions (5.11)]

6.1 Clinical Trials Experience

Because clinical trials are conducted under widely varying conditions, adverse reaction rates observed in the clinical trials of a drug cannot be directly compared to rates in the clinical trials of another drug and may not reflect the rates observed in practice.

At the usual maintenance dose (400 mg/day) and above, amiodarone hydrochloride causes adverse reactions in about three-fourths of all patients, resulting in discontinuation in 7 to 18%.

In surveys of almost 5,000 patients treated in open U.S. studies and in published reports of treatment with amiodarone hydrochloride, the adverse reactions most frequently requiring discontinuation of amiodarone hydrochloride included pulmonary infiltrates or fibrosis, paroxysmal ventricular tachycardia, congestive heart failure, and elevation of liver enzymes. Other symptoms causing discontinuations less often included visual disturbances, photosensitivity, blue skin discoloration, hyperthyroidism, and hypothyroidism.

The following side-effect rates are based on a retrospective study of 241 patients treated for 2 to 1,515 days (mean 441.3 days):

Thyroid

Common: Hypothyroidism, hyperthyroidism.

Cardiovascular

Common: Congestive heart failure, cardiac arrhythmias, SA node dysfunction.

Gastrointestinal

Very common: Nausea, vomiting.

Common: Constipation, anorexia, abdominal pain.

Dermatologic

Common: Solar dermatitis/photosensitivity.

Neurologic

Common: Malaise and fatigue, tremor/abnormal involuntary movements, lack of coordination, abnormal gait/ataxia, dizziness, paresthesias, decreased libido, insomnia, headache, sleep disturbances.

Ophthalmic

Common: Visual disturbances.

Hepatic

Common: Abnormal liver-function tests, nonspecific hepatic disorders.

Respiratory

Common: Pulmonary inflammation or fibrosis.

Other

Common: Flushing, abnormal taste and smell, edema, abnormal salivation, coagulation abnormalities.

Uncommon: Blue skin discoloration, rash, spontaneous ecchymosis, alopecia, hypotension, and cardiac conduction abnormalities.

6.2 Postmarketing Experience

The following adverse reactions have been identified during post-approval use of amiodarone hydrochloride. Because these reactions are reported voluntarily from a population of uncertain size, it is not always possible to reliably estimate their frequency or establish a causal relationship to drug exposure.

Hematologic: hemolytic anemia, aplastic anemia, pancytopenia, neutropenia, thrombocytopenia, agranulocytosis, granuloma.

Immune: anaphylactic/anaphylactoid reaction (including shock), angioedema.

Neurologic: pseudotumor cerebri, parkinsonian symptoms such as akinesia and bradykinesia (sometimes reversible with discontinuation of therapy), demyelinating polyneuropathy.

Psychiatric: hallucination, confusional state, disorientation, delirium.

Cardiac: hypotension (sometimes fatal), sinus arrest.

Respiratory: eosinophilic pneumonia, acute respiratory distress syndrome in the post-operative setting, bronchospasm, bronchiolitis obliterans organizing pneumonia, pulmonary alveolar hemorrhage, pleural effusion, pleuritis.

Gastrointestinal: pancreatitis, acute pancreatitis.

Hepatic: hepatitis, cholestatic hepatitis, cirrhosis.

Skin and Subcutaneous Tissue Disorders: urticaria, toxic epidermal necrolysis (sometimes fatal), erythema multiforme, Stevens-Johnson syndrome, exfoliative dermatitis, bullous dermatitis, drug rash with eosinophilia and systemic symptoms (DRESS), eczema, pruritus, skin cancer, lupus-like syndrome.

Musculoskeletal: myopathy, muscle weakness, rhabdomyolysis.

Renal: renal impairment, renal insufficiency, acute renal failure.

Reproductive: epididymitis, impotence.

Body as a whole: fever, dry mouth.

Endocrine and metabolic: thyroid nodules/ thyroid cancer, syndrome of inappropriate antidiuretic hormone secretion (SIADH).

Vascular: vasculitis.

7 DRUG INTERACTIONS

Because of amiodarone’s long half-life, expect drug interactions to persist for weeks to months after discontinuation of amiodarone.

Drug interactions with amiodarone are described in Table 1 below.

Table 1: Amiodarone Drug Interactions

Concomitant Drug Class/Name | Examples | Clinical Comment
Pharmacodynamic Interactions
QT Prolonging Drugs | class I and III antiarrhythmics,lithium, certain phenothiazines,tricyclicantidepressants,certainfluoroquinoloneandmacrolideantibiotics, azole antifungals,halogenatedinhalationanestheticagents | Increasedrisk of Torsade de Pointes.Avoidconcomitantuse.
Negative Chronotropes | digoxin, beta blockers,verapamil,diltiazem,clonidine,ivabradine | Potentiatestheelectrophysiologicandhemodynamiceffects of amiodarone, resultinginbradycardia, sinusarrest,andAVblock. Monitor heartrate.
Pharmacokinetic Interactions
CYP450 Inhibitors | grapefruitjuice,certainfluoroquinoloneandmacrolideantibiotics, azole antifungals,cimetidine,certain protease inhibitors | Increasedexposure of amiodarone. Avoidconcomitant use.
CYP450 Inducers | St.John’sWort | Reducedamiodarone serum levels.
Cyclosporine |  | Increasedplasmalevelsofcyclosporinehave been reported resultinginelevatedcreatinine,despitereduction of cyclosporinedose. Monitorcyclosporinedruglevelsand renal functionwithconcomitant use.
Cholestyramine |  | Reducedamiodarone serum levels.
Antiarrhythmics | quinidine,procainamide,flecainide | Reserveconcomitantuseforpatientswho are unresponsiveto a singleagent.Antiarrhythmicmetabolisminhibitedbyamiodarone.Initiateantiarrhythmic at a lowerthanusual dose and monitorpatientcarefully. Reduce dose levels of previouslyadministeredantiarrhythmic by 30 to 50% forseveraldaysaftertransitioningto oral amiodarone.Evaluatecontinuedneedforantiarrhythmic.
Digoxin |  | Increaseddigoxinconcentration.Reducedigoxinby half or discontinue. If continued,monitorforevidenceoftoxicity.
HMG-CoA ReductaseInhibitors | simvastatin,lovastatin,atorvastatin | Increasedplasma concentration of HMG-CoA reductaseinhibitor. Limitthe dose of lovastatinto 40 mg.Limit the coadministered dose of simvastatinto 20 mg. Lowerstarting dose of other CYP3A4substratesmay be required.
Warfarin |  | Potentiatesanticoagulant response and can resultinserious or fatalbleeding.Coadministrationincreasesprothrombintimeby 100% after 3 to 4 days.Reducewarfarin dose byone-thirdtoone-halfandmonitorprothrombin times.
Phenytoin |  | Increasedsteady-state levels of phenytoin.Monitorphenytoin levels.
Hepatitis C DirectActingAntiviral | sofosbuvir | Casesofsymptomaticbradyarrhythmiarequiringpacemaker insertion have been reported inpatientson oral maintenanceamiodaronewhoinitiatedtherapywithsofosbuvir.
CYP3A Substrate | lidocaine | Sinus bradycardia has been reported with oral amiodarone in combination with lidocaine given for local anesthesia. Monitor heart rate. A lower starting dose of lidocaine may be required.
CYP3A Substrate | fentanyl | Fentanyl in combination with amiodarone may cause hypotension, bradycardia, and decreased cardiac output.

8 USE IN SPECIFIC POPULATIONS

8.1 Pregnancy

Risk Summary

Available data from postmarketing reports and published case series indicate that amiodarone use in pregnant women may increase the risk for fetal adverse effects including neonatal hypo- and hyperthyroidism, neonatal bradycardia, neurodevelopmental abnormalities, preterm birth and fetal growth restriction. Amiodarone and its metabolite, desethylamiodarone (DEA), cross the placenta. Untreated underlying arrhythmias, including ventricular arrhythmias, during pregnancy pose a risk to the mother and fetus (see Clinical Considerations). In animal studies, administration of amiodarone to rabbits, rats, and mice during organogenesis resulted in embryo- fetal toxicity at doses less than the maximum recommended human maintenance dose (see Data). Advise pregnant women of the potential risk to a fetus.
The estimated background risk of major birth defects and miscarriage for the indicated population is unknown. All pregnancies have a background risk of birth defect, loss or other adverse outcomes. In the U.S. general population, the estimated background risk of major birth defects and miscarriage in clinically recognized pregnancies is 2% to 4% and 15% to 20%, respectively.

Clinical Considerations
Disease-associated maternal and or embryo/fetal Risk

The incidence of ventricular tachycardia is increased and may be more symptomatic during pregnancy. Ventricular arrhythmias most often occur in pregnant women with underlying cardiomyopathy, congenital heart disease, valvular heart disease, or mitral valve prolapse. Most tachycardia episodes are initiated by ectopic beats and the occurrence of arrhythmia episodes may therefore, increase during pregnancy due to the increased propensity to ectopic activity. Breakthrough arrhythmias may also occur during pregnancy, as therapeutic treatment levels may be difficult to maintain due to the increased volume of distribution and increased drug metabolism inherent in the pregnant state.

Fetal/Neonatal adverse reactions

Amiodarone and its metabolite have been shown to cross the placenta. Adverse fetal effects associated with maternal amiodarone use during pregnancy may include neonatal bradycardia, QT prolongation, and periodic ventricular extrasystoles, neonatal hypothyroidism (with or without goiter) detected antenatally or in the newborn and reported even after a few days of exposure, neonatal hyperthyroxinemia, neurodevelopmental abnormalities independent of thyroid function, including speech delay and difficulties with written language and arithmetic, delayed motor development, and ataxia, jerk nystagmus with synchronous head titubation, fetal growth restriction, and premature birth. Monitor the newborn for signs and symptoms of thyroid disorder and cardiac arrhythmias.

Labor and Delivery

Risk of arrhythmias may increase during labor and delivery. Patients treated with amiodarone hydrochloride should be monitored continuously during labor and delivery [see Warnings and Precautions (5.4)] .

Data

Animal Data

In pregnant rats and rabbits during the period of organogenesis, amiodarone hydrochloride in doses of 25 mg/kg/day (approximately 0.4 and 0.9 times, respectively, the maximum recommended human maintenance dose*) had no adverse effects on the fetus. In the rabbit, 75 mg/kg/day (approximately 2.7 times the maximum recommended human maintenance dose*) caused abortions in greater than 90% of the animals. In the rat, doses of 50 mg/kg/day or more were associated with slight displacement of the testes and an increased incidence of incomplete ossification of some skull and digital bones; at 100 mg/kg/day or more, fetal body weights were reduced; at 200 mg/kg/day, there was an increased incidence of fetal resorption. (These doses in the rat are approximately 0.8, 1.6 and 3.2 times the maximum recommended human maintenance dose*) Adverse effects on fetal growth and survival also were noted in one of two strains of mice at a dose of 5 mg/kg/day (approximately 0.04 times the maximum recommended human maintenance dose*).

*600 mg in a 60 kg patient (doses compared on a body surface area basis)

8.2 Lactation

Risk Summary
Amiodarone and one of its major metabolites, DEA, are present in breastmilk at between 3.5% and 45% of the maternal weight- adjusted dosage of amiodarone. There are cases of hypothyroidism and bradycardia in breastfed infants, although it is unclear if these effects are due to amiodarone exposure in breastmilk. Breastfeeding is not recommended during treatment with amiodarone hydrochloride [see Warnings and Precautions (5.6, 5.7)].

8.3 Females and Males of Reproductive Potential

Infertility
Based on animal fertility studies, amiodarone hydrochloride may reduce female and male fertility. It is not known if this effect is reversible. [see Nonclinical Toxicology (13.1)].

8.4 Pediatric Use

The safety and effectiveness of amiodarone hydrochloride in pediatric patients have not been established.

8.5 Geriatric Use

Normal subjects over 65 years of age show lower clearances and increased drug half-life than younger subjects [see Clinical Pharmacology (12.3)] . In general, dose selection for an elderly patient should be cautious, usually starting at the low end of the dosing range, reflecting the greater frequency of decreased hepatic, renal, or cardiac function, and of concomitant disease or other drug therapy.

10 OVERDOSAGE

There have been cases, some fatal, of amiodarone hydrochloride overdose.

Monitor the patient’s cardiac rhythm and blood pressure, and, if bradycardia ensues, a β-adrenergic agonist or a pacemaker may be used. Treat hypotension with inadequate tissue perfusion with positive inotropic and vasopressor agents. Neither amiodarone hydrochloride nor its metabolite is dialyzable.

11 DESCRIPTION

Amiodarone hydrochloride tablets, USP is an antiarrhythmic drug, available for oral administration as white to off-white, scored tablets containing 200 mg of amiodarone hydrochloride USP. The inactive ingredients present are colloidal silicon dioxide, lactose monohydrate, magnesium stearate, povidone, and sodium starch glycolate. Amiodarone hydrochloride is a benzofuran derivative: 2-butyl-3-benzofuranyl 4-[2-(diethylamino)-ethoxy]- 3,5-diiodophenyl ketone hydrochloride.

The structural formula is as follows:

Amiodarone hydrochloride USP is a white or almost white, fine crystalline powder. It is slightly soluble in water, soluble in alcohol, and freely soluble in chloroform. It contains 37.3% iodine by weight.

12 CLINICAL PHARMACOLOGY

12.1 Mechanism of Action

Amiodarone is considered a class III antiarrhythmic drug, but it possesses electrophysiologic characteristics of all four Vaughan Williams classes. Like class I drugs, amiodarone blocks sodium channels at rapid pacing frequencies, and like class II drugs, amiodarone exerts a noncompetitive antisympathetic action. One of its main effects, with prolonged administration, is to lengthen the cardiac action potential, a class III effect. The negative chronotropic effect of amiodarone in nodal tissues is similar to the effect of class IV drugs. In addition to blocking sodium channels, amiodarone blocks myocardial potassium channels, which contributes to slowing of conduction and prolongation of refractoriness. The antisympathetic action and the block of calcium and potassium channels are responsible for the negative dromotropic effects on the sinus node and for the slowing of conduction and prolongation of refractoriness in the atrioventricular (AV) node. Its vasodilatory action can decrease cardiac workload and consequently myocardial oxygen consumption.

Amiodarone hydrochloride prolongs the duration of the action potential of all cardiac fibers while causing minimal reduction of dV/dt (maximal upstroke velocity of the action potential). The refractory period is prolonged in all cardiac tissues. Amiodarone hydrochloride increases the cardiac refractory period without influencing resting membrane potential, except in automatic cells where the slope of the prepotential is reduced, generally reducing automaticity. These electrophysiologic effects are reflected in a decreased sinus rate of 15 to 20%, increased PR and QT intervals of about 10%, the development of U-waves, and changes in T-wave contour. These changes should not require discontinuation of amiodarone hydrochloride as they are evidence of its pharmacological action, although amiodarone hydrochloride can cause marked sinus bradycardia or sinus arrest and heart block [see Warnings and Precautions (5.4)].

Hemodynamics

In animal studies and after intravenous administration in man, amiodarone hydrochloride relaxes vascular smooth muscle, reduces peripheral vascular resistance (afterload), and slightly increases cardiac index. After oral dosing, however, amiodarone hydrochloride produces no significant change in left ventricular ejection fraction (LVEF), even in patients with depressed LVEF. After acute intravenous dosing in man, amiodarone hydrochloride may have a mild negative inotropic effect.

12.2 Pharmacodynamics

There is no well-established relationship between plasma concentration and effectiveness, but it does appear that concentrations much below 1 mg/L are often ineffective and that levels above 2.5 mg/L are generally not needed. Plasma-concentration measurements can be used to identify patients whose levels are unusually low, and who might benefit from a dose increase, or unusually high, and who might have dosage reduction in the hope of minimizing side effects.

Effects on abnormal rhythms are not seen before 2 to 3 days and usually require 1 to 3 weeks, even when a loading dose is used. There may be a continued increase in effect for longer periods still. There is evidence that the time to effect is shorter when a loading-dose regimen is used.

Consistent with the slow rate of elimination, antiarrhythmic effects persist for weeks or months after amiodarone hydrochloride is discontinued, but the time of recurrence is variable and unpredictable. In general, when the drug is resumed after recurrence of the arrhythmia, control is established relatively rapidly compared to the initial response, presumably because tissue stores were not wholly depleted.

12.3 Pharmacokinetics

Absorption
Following oral administration in humans, amiodarone hydrochloride is slowly and variably absorbed. The bioavailability of amiodarone hydrochloride is approximately 50%. Maximum plasma concentrations are attained 3 to 7 hours after a single dose. Plasma concentrations with chronic dosing at 100 to 600 mg/day are approximately dose proportional, with a mean 0.5 mg/L increase for each 100 mg/day. These means, however, include considerable individual variability.

Food increases the rate and extent of absorption of amiodarone hydrochloride. The effects of food upon the bioavailability of amiodarone hydrochloride have been studied in 30 healthy subjects who received a single 600 mg dose immediately after consuming a high-fat meal and following an overnight fast. The area under the plasma concentration-time curve (AUC) and the peak plasma concentration (Cmax) of amiodarone increased by 2.3 (range 1.7 to 3.6) and 3.8 (range 2.7 to 4.4) times, respectively, in the presence of food. Food also increased the rate of absorption of amiodarone, decreasing the time to peak plasma concentration (Tmax) by 37%. The mean AUC and mean Cmaxof the major metabolite of amiodarone, DEA increased by 55% (range 58 to 101%) and 32% (range 4 to 84%), respectively, but there was no change in the Tmaxin the presence of food.

Distribution

Amiodarone hydrochloride is highly protein-bound (approximately 96%). Amiodarone hydrochloride has a very large but variable volume of distribution, averaging about 60 L/kg, because of extensive accumulation in various sites, especially adipose tissue and highly perfused organs, such as the liver, lung, and spleen.

One major metabolite of amiodarone hydrochloride, DEA, has been identified in man; it accumulates to an even greater extent in almost all tissues. No data are available on the activity of DEA in humans, but in animals, it has significant electrophysiologic and antiarrhythmic effects generally similar to amiodarone itself. DEA’s precise role and contribution to the antiarrhythmic activity of oral amiodarone are not certain. The development of maximal ventricular class III effects after oral amiodarone hydrochloride administration in humans correlates more closely with DEA accumulation over time than with amiodarone accumulation.

Elimination
Following single dose administration in 12 healthy subjects, amiodarone hydrochloride exhibited multi-compartmental pharmacokinetics with a mean apparent plasma terminal elimination half-life of 58 days (range 15 to 142 days) for amiodarone and 36 days (range 14 to 75 days) for the active metabolite (DEA). In patients, following discontinuation of chronic oral therapy, amiodarone hydrochloride has been shown to have a biphasic elimination with an initial 50% reduction of plasma levels after 2.5 to 10 days. A much slower terminal plasma- elimination phase shows a half-life of the parent compound ranging from 26 to 107 days, with a mean of approximately 53 days and most patients in the 40- to 55-day range. In the absence of a loading-dose period, steady-state plasma concentrations, at constant oral dosing, would therefore be reached between 130 and 535 days, with an average of 265 days. For the metabolite, the mean plasma- elimination half-life was approximately 61 days. These data probably reflect an initial elimination of drug from well-perfused tissue (the 2.5- to 10-day half-life phase), followed by a terminal phase representing extremely slow elimination from poorly perfused tissue compartments such as fat.

The considerable inter-subject variation in both phases of elimination, as well as uncertainty as to what compartment is critical to drug effect, requires attention to individual responses once arrhythmia control is achieved with loading doses because the correct maintenance dose is determined, in part, by the elimination rates. Individualize maintenance doses of amiodarone hydrochloride [see Dosage and Administration (2)].

Metabolism

Amiodarone is metabolized to DEA by the cytochrome P450 (CYP) enzyme group, specifically CYP3A and CYP2C8. The CYP3A isoenzyme is present in both the liver and intestines. In vitro, amiodarone and DEA exhibit a potential to inhibit CYP2C9, CYP2C19, CYP2D6, CYP3A, CYP2A6, CYP2B6 and CYP2C8. Amiodarone and DEA have also a potential to inhibit some transporters such as P-glycoprotein and organic cation transporter (OCT2).

Excretion
Amiodarone is eliminated primarily by hepatic metabolism and biliary excretion and there is negligible excretion of amiodarone or DEA in urine. Neither amiodarone nor DEA is dialyzable.
Specific Populations
Effect of Age : Normal subjects over 65 years of age show lower clearances (about 100 mL/hr/kg) than younger subjects (about 150 mL/hr/kg) and an increase in t½ from about 20 to 47 days.

Renal Impairment: Renal impairment does not influence the pharmacokinetics of amiodarone or DEA.

Hepatic Impairment: After a single dose of intravenous amiodarone to cirrhotic patients, significantly lower Cmax and average concentration values are seen for DEA, but mean amiodarone levels are unchanged.

Cardiac Disease: In patients with severe left ventricular dysfunction, the pharmacokinetics of amiodarone are not significantly altered but the terminal elimination t½ of DEA is prolonged.

Although no dosage adjustment for patients with renal, hepatic, or cardiac abnormalities has been defined during chronic treatment with oral amiodarone, close clinical monitoring is prudent for elderly patients and those with severe left ventricular dysfunction.

Drug Interactions:

Effects of other agents on amiodarone

Grapefruit juice: Grapefruit juice given to healthy volunteers increased amiodarone AUC by 50% and Cmaxby 84%, and decreased DEA to unquantifiable concentrations.

Cimetidineinhibits CYP3A and can increase serum amiodarone levels.

Cholestyraminereduces enterohepatic circulation of amiodarone thereby increasing its elimination. This results in reduced amiodarone serum levels and half-life.

Effects of amiodarone on agents:

CYP3A substrates:

Amiodarone taken concomitantly with quinidineincreases the quinidine serum concentration by 33% after two days. Amiodarone taken concomitantly with procainamidefor less than seven days increases plasma concentrations of procainamide and n-acetyl procainamide by 55% and 33%, respectively.

Loratadine, a non-sedating antihistaminic, is metabolized primarily by CYP3A and its metabolism can be inhibited by amiodarone.

Metabolism of lidocainecan be inhibited by amiodarone.

Cyclophosphamideis a prodrug, metabolized by CYP450 including CYP3A to an active metabolite. The metabolism of cyclophosphamide may be inhibited by amiodarone.

Clopidogrel, an inactive thienopyridine prodrug, is metabolized in the liver by CYP3A to an active metabolite. A potential interaction between clopidogrel and amiodarone resulting in ineffective inhibition of platelet aggregation has been reported.

Macrolide/ketolide antibiotics:
Amiodarone can inhibit the metabolism of macrolide/ketolide antibiotics(except for azithromycin) and systemic azole antifungal drugs.

P-glycoprotein substrates:
Amiodarone taken concomitantly with digoxinincreases the serum digoxin concentration by 70% after one day.

Dabigatran etexilatewhen taken concomitantly with oral amiodarone can result in elevated serum concentration of dabigatran.

Dextromethorphanis a substrate for both CYP2D6 and CYP3A. Amiodarone inhibits CYP2D6. Chronic (> 2 weeks) oral amiodarone administration impairs metabolism of dextromethorphan can lead to increased serum concentrations.

13 NONCLINICAL TOXICOLOGY

13.1 Carcinogenesis, Mutagenesis, Impairment of Fertility

Amiodarone hydrochloride was associated with a statistically significant, dose-related increase in the incidence of thyroid tumors (follicular adenoma and/or carcinoma) in rats. The incidence of thyroid tumors was greater than control at the lowest dose level tested, i.e., 5 mg/kg/day (approximately 0.08 times the maximum recommended human maintenance dose*).

Mutagenicity studies (Ames, micronucleus, and lysogenic tests) with amiodarone hydrochloride were negative.

In a study in which amiodarone hydrochloride was administered to male and female rats, beginning 9 weeks prior to mating, reduced fertility was observed at a dose level of 90 mg/kg/day (approximately 1.4 times the maximum recommended human maintenance dose*).

*600 mg in a 60 kg patient (dose compared on a body surface area basis)

16 HOW SUPPLIED/STORAGE AND HANDLING

Amiodarone Hydrochloride Tablets USP, 200 mg are white to off-white, round biconvex uncoated tablets debossed with “8” and “4” separated by a breakline on one side and “A” on the other side.

NDC: 70518-1939-00

NDC: 70518-1939-01

PACKAGING: 30 in 1 BLISTER PACK

PACKAGING: 90 in 1 BOTTLE PLASTIC

Keep tightly closed.

Store at 20° to 25°C (68° to 77°F) [see USP Controlled Room Temperature].

Protect from light.

Dispense in a light-resistant, tight container.

Repackaged and Distributed By:

Remedy Repack, Inc.

625 Kolter Dr. Suite #4 Indiana, PA 1-724-465-8762

17 PATIENT COUNSELING INFORMATION

Advise the patient to read the FDA-approved patient labeling (Medication Guide).

Advise pregnant women of the potential risk to a fetus. Advise females of reproductive potential to inform their prescriber of a known or suspected pregnancy [see Use in Specific Populations (8.1)].

Advise women that breastfeeding is not recommended during treatment with amiodarone hydrochloride tablets [see Use in Specific Populations (8.2)].

Advise patients to avoid grapefruit juice and St. John's Wort.

Advise patients to seek medical attention if they experience the signs and symptoms of pulmonary toxicity, worsening arrhythmia, bradycardia, visual impairment, or hypo- and hyperthyroidism.

Dispense with Medication Guide available at: www.aurobindousa.com/medication-guides.

Distributed by:
Aurobindo Pharma USA, Inc.
279 Princeton-Hightstown Road
East Windsor, NJ 08520
Manufactured by:
Aurobindo Pharma Limited
Hyderabad-500 032, India
Revised: 10/2022

Repackaged By / Distributed By: RemedyRepack Inc.

625 Kolter Drive, Indiana, PA 15701

(724) 465-8762

MEDICATION GUIDE

Amiodarone Hydrochloride Tablets, USP

(A-mee-OH-da-rone HYE-droe-KLOR-ide)

What is the most important information I should know about amiodarone hydrochloridetablets?

Amiodarone hydrochloridetablets can cause serious side effects that can lead to death, including:

- lung problems
- liver problems
- worsening of heartbeat problems

Call your healthcare provider or get medical help right away if you have any of the following symptoms during treatment with amiodarone hydrochloridetablets:

- trouble breathing, wheezing, shortness of breath, coughing chest pain, spitting up of blood, or fever
- nausea or vomiting, brown or dark-colored urine, feel more tired than usual, yellowing of your skin or the whites of your eyes (jaundice), or right upper stomach-area pain
- heart pounding, skipping a beat, beating fast or slowly, feel light-headed, or if you faint
- vision problems, including blurred vision, see halos, or your eyes become sensitive to light. You should have regular eye exams before and during treatment with amiodarone hydrochloride tablets.

Amiodarone hydrochloride tablets should be started in a hospital so that your medical condition can be carefully monitored.

Amiodarone hydrochloride tablets should only be used to treat people who have been diagnosed with life-threatening heartbeat problems called ventricular arrhythmias, when other treatments did not work or you cannot tolerate them.

Amiodarone hydrochloridetablets can cause other serious side effects. See “What are the possible side effects of amiodarone hydrochloridetablets?” If you get serious side effects during treatment you may need to stop amiodarone hydrochloride tablets, have your dose changed, or get medical treatment. Talk with your healthcare provider before you stop taking amiodarone hydrochloride tablets.

You may still have side effects after stopping amiodarone hydrochloride tablets because the medicine stays in your body for months after treatment is stopped.

You should have regular check-ups, blood tests, chest x-rays before and during treatment with amiodarone hydrochloride tablets to check for serious side effects. You should also have lung function tests before starting treatment with amiodarone hydrochloride tablets.

What are amiodarone hydrochloridetablets?

Amiodarone hydrochloride tablets are a prescription medicine used to treat people who have been diagnosed with life-threatening heartbeat problems called ventricular arrhythmias, when other treatments did not work or you cannot tolerate them.

It is not known if amiodarone hydrochloride tablets are safe and effective in children.

Who should not take amiodarone hydrochloridetablets?

Do not take amiodarone hydrochloridetablets if you:

- have a serious heart problem called cardiogenic shock
- have certain types of the heart condition called heart block, with or without a slow heart rate
- have a slow heart rate with dizziness or lightheadedness, and you do not have an implanted pacemaker
- are allergic to amiodarone, iodine, or any of the other ingredients in amiodarone hydrochloride tablets. See the end of this Medication Guide for a complete list of ingredients in amiodarone hydrochloride tablets.

Before taking amiodarone hydrochloridetablets, tell your healthcare provider about all of your medical conditions, including if you:

- have lung or breathing problems
- have liver problems
- have or had thyroid problems
- have a slow heart rate or blood pressure problems
- have diarrhea or have had diarrhea for a long period of time
- have been told that you have low levels of potassium, magnesium, or calcium in your blood
- have an implanted pacemaker or defribrillator
- if you plan to have surgery with general anesthesia
- are pregnant or plan to become pregnant. Amiodarone hydrochloride tablets may harm your unborn baby. Tell your healthcare provider right away if you become pregnant during treatment with amiodarone hydrochloride tablets. Amiodarone hydrochloride can stay in your body for months after treatment is stopped.
- are breastfeeding or plan to breastfeed. Amiodarone hydrochloride can pass into your breast milk and may harm your baby. You should not breast feed while taking amiodarone hydrochloride tablets. Amiodarone hydrochloride tablets can stay in your body for months after treatment is stopped. Talk to your healthcare provider about the best way to feed your baby during this time.

Tell your healthcare provider about all the medicines you take including prescription and over-the-counter medicines, vitamins, and herbal supplements. Amiodarone hydrochloride tablets and certain other medicines can affect with each other and cause serious side effects. You can ask your pharmacist for a list of medicines that interact with amiodarone hydrochloride tablets.

How should I take amiodarone hydrochloridetablets?

- When you are discharged from the hospital, take amiodarone hydrochloride tablets exactlyas your doctor tells you to take it.
- Your healthcare provider will tell you how much amiodarone hydrochloride tablets to take and when to take it.
- Your healthcare provider may change your dose of amiodarone hydrochloride tablets as needed if your heart rhythm is controlled, or if you have certain side effects. Your healthcare provider should monitor you carefully when your dose of amiodarone hydrochloride tablets are being changed.
- Take your dose of amiodarone hydrochloridetablets the same way each time, either with or without food.
- If you take too much amiodarone hydrochloride tablets, call your healthcare provider or go to the nearest hospital emergency room right away. If you miss a dose, wait and take your next dose at your regular time. Do not take two doses at the same. Continue with your next regularly scheduled dose.

What should I avoid while taking amiodarone hydrochloridetablets?

- Avoid drinking grapefruit juice during treatment with amiodarone hydrochloride tablets. Drinking grapefruit juice with amiodarone hydrochloride tablets may increase the amount of amiodarone hydrochloride in your blood, and this may lead to side effects.
- Amiodarone hydrochloride tablets can make your skin sensitive to sunlight. You could get severe sunburn. Use sunscreen and wear a hat and clothes that cover your skin to help protect you if you must be in sunlight. Talk to your healthcare if you get a sunburn. See “Skin problems” in the Medication Guide section “What are the possible side effects of amiodarone hydrochloridetablets?”below.

What are the possible side effects of amiodaronehydrochloridetablets?

Amiodarone hydrochloridetablets can cause serious side effects, including:

- See “What is the most important information I should know about amiodarone hydrochloridetablets?”
- Nerve problems. Amiodarone hydrochloride tablets can cause nerve problems. Call your healthcare provider if you develop symptoms of nerve problems, including: a feeling of “pins and needles” or numbness in your hands, legs, or feet, muscle weakness, uncontrolled movements, poor coordination, or trouble walking.
- Skin problems. Amiodarone hydrochloride tablets can cause your skin to be more sensitive to the sun or turn a bluish-gray color. People who have fair skin or people who have a lot of sun exposure may be more at risk for these skin problems. Some of the bluish-gray skin color may return to normal after stopping amiodarone hydrochloride tablets.
- Thyroid problems. Amiodarone hydrochloride tablets can cause you to have either decreased thyroid function (hypothyroidism), which can sometimes be severe, or an overactive thyroid (hyperthyroidism), which can be severe.
  - If you develop decreased thyroid function during treatment with amiodarone hydrochloride tablets, your healthcare provider may need to reduce your dose or stop your treatment with amiodarone hydrochloride tablets, and possibly prescribe medicine to replace your thyroid hormone.
  - An overactive thyroid can cause you to produce too much thyroid hormone. You can have abnormal heartbeats even while you are receiving amiodarone hydrochloride tablets. Your healthcare provider may prescribe certain medicines to treat your overactive thyroid. Call your healthcare provider if you get any abnormal heart beats during treatment with amiodarone hydrochloride tablets. This may mean that you have an overactive thyroid.
  - Your healthcare provider should do tests to check your thyroid function before you start and during treatment with amiodarone hydrochloride tablets.
  - Call your healthcare provider if you develop any of the following symptoms of a thyroid problem during treatment with amiodarone hydrochloride tablets:
    - weakness
    - weight loss or weight gain
    - heat or cold intolerance
    - hair thinning
    - sweating
    - changes in your menstrual periods
    - swelling of your neck (goiter)
    - nervousness
    - irritability
    - restlessness
    - decreased concentration
    - feeling depressed (in the elderly)
    - tremor

The most common side effects of amiodarone hydrochloride tablets include:

- lung problems

- heartbeat problems
- heart problems
- liver problems

Amiodarone hydrochloride tablets may affect fertility in males and females. It is not known if the effects are reversible. Talk to your healthcare provider if you have concerns about fertility.

These are not all the possible side effects of amiodarone hydrochloride tablets. For more information, ask your healthcare provider or pharmacist.

Call your doctor for medical advice about side effects. You may report side effects to FDA at 1-800-FDA-1088.

How should I store amiodarone hydrochloridetablets?

- Store amiodarone hydrochloride tablets at room temperature between 20° to 25°C (68° to 77°F).
- Keep amiodarone hydrochloride tablets in a tightly closed container, and keep amiodarone hydrochloride tablets out of the light.

Keep amiodarone hydrochloridetablets and all medicines out of the reach of children.

General information about the safe and effective use of amiodarone hydrochloridetablets

Medicines are sometimes prescribed for purposes other than those listed in a Medication Guide. Do not use amiodarone hydrochloride tablets for a condition for which it was not prescribed. Do not give amiodarone hydrochloride tablets to other people, even if they have the same symptoms that you have. They may harm them. You can ask your pharmacist or healthcare provider for information about amiodarone hydrochloride tablets that is written for health professionals.

What are the ingredients in amiodarone hydrochloridetablets?

Active Ingredient: amiodarone hydrochloride

Inactive Ingredients: colloidal silicon dioxide, lactose monohydrate, magnesium stearate, povidone, and sodium starch glycolate.

For more information, call Aurobindo Pharma USA, Inc. at 1-866-850-2876.

Dispense with Medication Guide available at: www.aurobindousa.com/medication-guides.

This Medication Guide has been approved by the U.S. Food and Drug Administration.

Distributed by:

Aurobindo Pharma USA, Inc.

279 Princeton-Hightstown Road

East Windsor, NJ 08520

Manufactured by:

Aurobindo Pharma Limited

Hyderabad-500 032, India

Revised: 10/2022

Repackaged By / Distributed By: RemedyRepack Inc.

625 Kolter Drive, Indiana, PA 15701

(724) 465-8762

PACKAGE LABEL

DRUG: Amiodarone Hydrochloride

GENERIC: Amiodarone Hydrochloride

DOSAGE: TABLET

ADMINSTRATION: ORAL

NDC: 70518-1939-0

NDC: 70518-1939-1

COLOR: white

SHAPE: ROUND

SCORE: Two even pieces

SIZE: 11 mm

IMPRINT: 8;4;A

PACKAGING: 30 in 1 BLISTER PACK

PACKAGING: 90 in 1 BOTTLE PLASTIC

ACTIVE INGREDIENT(S):

- AMIODARONE HYDROCHLORIDE 200mg in 1

INACTIVE INGREDIENT(S):

- SILICON DIOXIDE
- LACTOSE MONOHYDRATE
- MAGNESIUM STEARATE
- POVIDONE K30
- SODIUM STARCH GLYCOLATE TYPE A POTATO